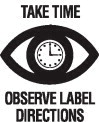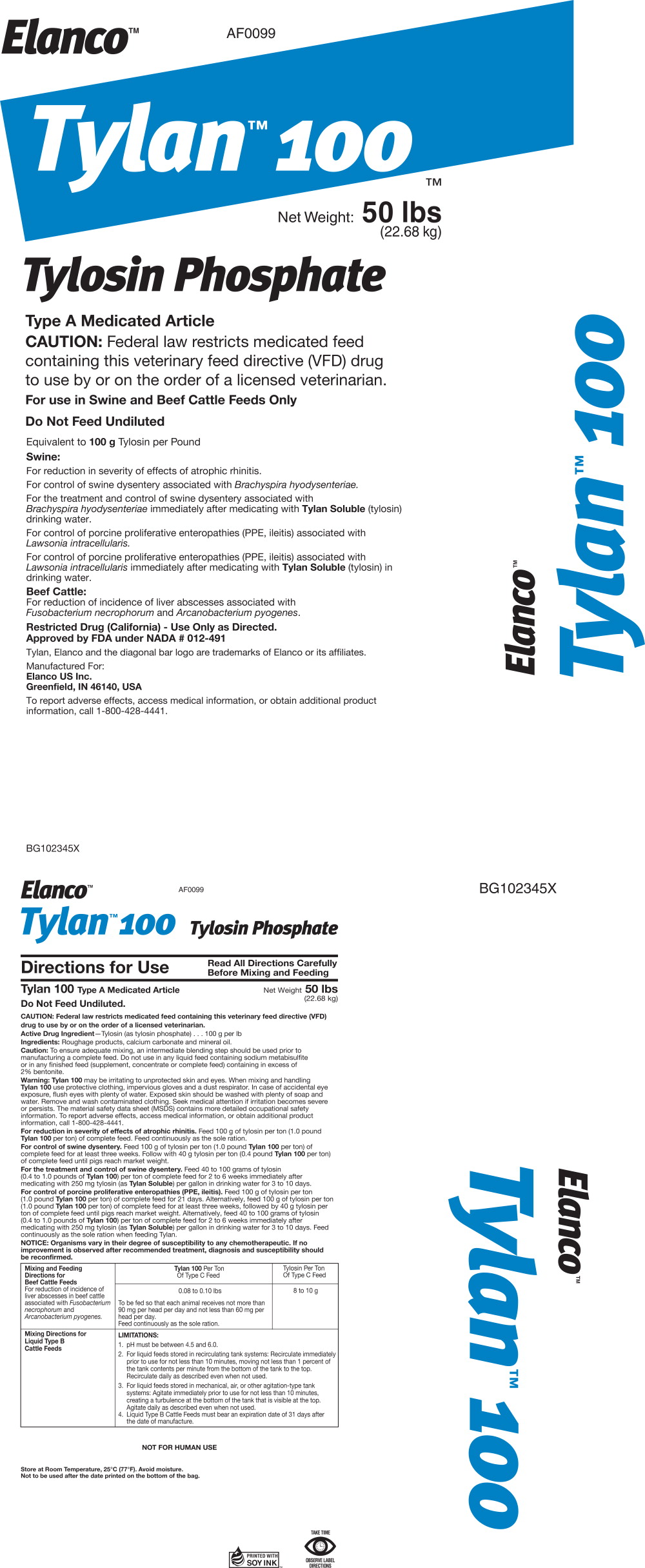 DRUG LABEL: Tylan 100
NDC: 58198-0099 | Form: GRANULE
Manufacturer: Elanco US Inc.
Category: animal | Type: VFD TYPE A MEDICATED ARTICLE ANIMAL DRUG LABEL
Date: 20260106

ACTIVE INGREDIENTS: tylosin phosphate 100 g/.45 kg

AF0099
BG102345X
Elanco™
Tylan™ 100

Net Weight: 50 lbs
(22.68 kg)

Tylosin Phosphate

Type A Medicated Article

CAUTION: Federal law restricts medicated feed containing this veterinary feed directive (VFD) drug to use by or on the order of a licensed veterinarian.

For use in Swine and Beef Cattle Feeds Only

Do Not Feed Undiluted

Equivalent to 100 g Tylosin per Pound

Swine:

For reduction in severity of effects of atrophic rhinitis.

For control of swine dysentery associated with Brachyspira hyodysenteriae.

For the treatment and control of swine dysentery associated with Brachyspira hyodysenteriae immediately after medicating with Tylan Soluble (tylosin) drinking water.

For control of porcine proliferative enteropathies (PPE, ileitis) associated with Lawsonia intracellularis.

For control of porcine proliferative enteropathies (PPE, ileitis) associated with Lawsonia intracellularis immediately after medicating with Tylan Soluble (tylosin) in drinking water.

Beef Cattle:

For reduction of incidence of liver abscesses associated with Fusobacterium necrophorum and Arcanobacterium pyogenes.

Restricted Drug (California) - Use Only as Directed.

Approved by FDA under NADA # 012-491

Tylan, Elanco and the diagonal bar logo are trademarks of Elanco or its affiliates.

Manufactured For:

Elanco US Inc.

Greenfield, IN 46140, USA

To report adverse effects, access medical information, or obtain additional product information, call 1-800-428-4441.

AF0099
BG102345X

Elanco™

Tylan™ 100 Tylosin Phosphate

Directions for Use

Read All Directions Carefully Before Mixing and Feeding

Tylan 100 Type A Medicated Article

Net Weight 50 lbs (22.68 kg)

Do Not Feed Undiluted.

CAUTION: Federal law restricts medicated feed containing this veterinary feed directive (VFD) drug to use by or on the order of a licensed veterinarian.

Active Drug Ingredient—Tylosin (as tylosin phosphate) . . . 100 g per lb

INACTIVE INGREDIENT

Ingredients: Roughage products, calcium carbonate and mineral oil.

Caution: To ensure adequate mixing, an intermediate blending step should be used prior to manufacturing a complete feed. Do not use in any liquid feed containing sodium metabisulfite or in any finished feed (supplement, concentrate or complete feed) containing in excess of 2% bentonite.

WARNINGS

Warning: Tylan 100 may be irritating to unprotected skin and eyes. When mixing and handling Tylan 100 use protective clothing, impervious gloves and a dust respirator. In case of accidental eye exposure, flush eyes with plenty of water. Exposed skin should be washed with plenty of soap and water. Remove and wash contaminated clothing. Seek medical attention if irritation becomes severe or persists. The material safety data sheet (MSDS) contains more detailed occupational safety information. To report adverse effects, access medical information, or obtain additional product information, call 1-800-428-4441.

For reduction in severity of effects of atrophic rhinitis. Feed 100 g of tylosin per ton (1.0 pound Tylan 100 per ton) of complete feed. Feed continuously as the sole ration.

For control of swine dysentery. Feed 100 g of tylosin per ton (1.0 pound Tylan 100 per ton) of complete feed for at least three weeks. Follow with 40 g tylosin per ton (0.4 pound Tylan 100 per ton) of complete feed until pigs reach market weight.

For the treatment and control of swine dysentery. Feed 40 to 100 grams of tylosin (0.4 to 1.0 pounds of Tylan 100) per ton of complete feed for 2 to 6 weeks immediately after medicating with 250 mg tylosin (as Tylan Soluble) per gallon in drinking water for 3 to 10 days.

For control of porcine proliferative enteropathies (PPE, ileitis). Feed 100 g of tylosin per ton (1.0 pound Tylan 100 per ton) of complete feed for 21 days. Alternatively, feed 100 g of tylosin per ton (1.0 pound Tylan 100 per ton) of complete feed for at least three weeks, followed by 40 g tylosin per ton of complete feed until pigs reach market weight. Alternatively, feed 40 to 100 grams of tylosin (0.4 to 1.0 pounds of Tylan 100) per ton of complete feed for 2 to 6 weeks immediately after medicating with 250 mg tylosin (as Tylan Soluble) per gallon in drinking water for 3 to 10 days. Feed continuously as the sole ration when feeding Tylan.

NOTICE: Organisms vary in their degree of susceptibility to any chemotherapeutic. If no improvement is observed after recommended treatment, diagnosis and susceptibility should be reconfirmed.

Mixing and Feeding Directions for Beef Cattle Feeds For reduction of incidence of liver abscesses in beef cattle associated with Fusobacterium necrophorum and Arcanobacterium pyogenes. | Tylan 100 Per Ton Of Type C Feed | Tylosin Per Ton Of Type C Feed
Mixing and Feeding Directions for Beef Cattle Feeds For reduction of incidence of liver abscesses in beef cattle associated with Fusobacterium necrophorum and Arcanobacterium pyogenes. | 0.08 to 0.10 lbs | 8 to 10 g
Mixing and Feeding Directions for Beef Cattle Feeds For reduction of incidence of liver abscesses in beef cattle associated with Fusobacterium necrophorum and Arcanobacterium pyogenes. | To be fed so that each animal receives not more than 90 mg per head per day and not less than 60 mg per head per day.
Mixing and Feeding Directions for Beef Cattle Feeds For reduction of incidence of liver abscesses in beef cattle associated with Fusobacterium necrophorum and Arcanobacterium pyogenes. | Feed continuously as the sole ration.
Mixing Directions for Liquid Type B Cattle Feeds | LIMITATIONS:; 1. pH must be between 4.5 and 6.0. 2. For liquid feeds stored in recirculating tank systems: Recirculate immediately prior to use for not less than 10 minutes, moving not less than 1 percent of the tank contents per minute from the bottom of the tank to the top. Recirculate daily as described even when not used. 3. For liquid feeds stored in mechanical, air, or other agitation-type tank systems: Agitate immediately prior to use for not less than 10 minutes, creating a turbulence at the bottom of the tank that is visible at the top. Agitate daily as described even when not used. 4. Liquid Type B Cattle Feeds must bear an expiration date of 31 days after the date of manufacture.

NOT FOR HUMAN USE

STORAGE AND HANDLING

Store at Room Temperature, 25°C (77°F). Avoid moisture.
Not to be used after the date printed on the bottom of the bag.

Principal Display Panel - 50 lbs Bag Label

Elanco™
Tylan™ 100™

Net Weight: 50 lbs
(22.68 kg)

Tylosin Phosphate

Type A Medicated Article